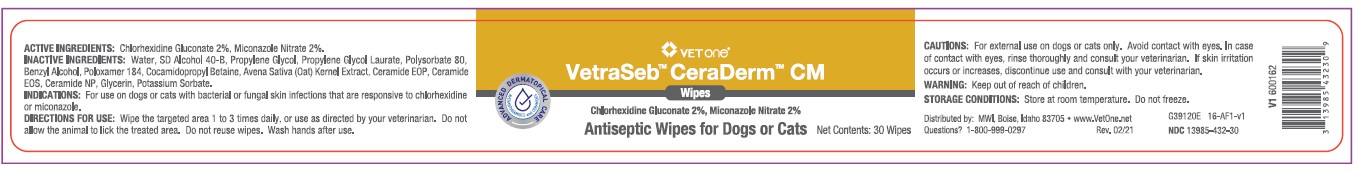 DRUG LABEL: VetraSeb CeraDerm
NDC: 13985-432 | Form: SWAB
Manufacturer: MWI/VETONE
Category: animal | Type: OTC ANIMAL DRUG LABEL
Date: 20210520

ACTIVE INGREDIENTS: CHLORHEXIDINE GLUCONATE 20 mg/1 1; MICONAZOLE NITRATE 20 mg/1 1
INACTIVE INGREDIENTS: WATER; ALCOHOL; PROPYLENE GLYCOL; PROPYLENE GLYCOL LAURATES; POLYSORBATE 80; BENZYL ALCOHOL; POLOXAMER 184; COCAMIDOPROPYL BETAINE; AVENANTHRAMIDES; CERAMIDE 1; CERAMIDE EOS; CERAMIDE NP; GLYCERIN; POTASSIUM SORBATE

DESCRIPTION

VetraSeb™ CeraDerm™ CM

Antiseptic Wipes for Dogs or Cats

ACTIVE INGREDIENTS: Chlorhexidine Gluconate 2%, Miconazole Nitrate 2%.

INACTIVE INGREDIENTS: Water, SD Alcohol 40-B, Propylene Glycol, Propylene Glycol Laurate, Polysorbate 80, Benzyl Alcohol, Poloxamer 184, Cocamidopropyl Betaine, Avena Sativa (Oat) Kernel Extract, Ceramide EOP, Ceramide EOS, Ceramide NP, Glycerin, Potasssium Sorbate.

INDICATIONS AND USAGE

INDICATIONS: For use on dogs or cats with bacterial or fungal skin infections that are responsive to chlorhexidine or miconazole.

DIRECTIONS FOR USE: Wipe the targeted area 1 to 3 times daily, or use as directed by your veterinarian. Do not allow the animal to lick the treated area. Do not reuse wipes. Wash hands after use.

WARNINGS AND PRECAUTIONS

CAUTIONS: For external use on dogs or cats only. Avoid contact with eyes. In case of contact with eyes, rinse thoroughly and consult your veterinarian. If skin irritation occurs or increases, discontinue use and consult with your veterinarian.

WARNING: Keep out of reach of children.

STORAGE AND HANDLING

STORAGE CONDITIONS: Store at room temperature. Do not freeze.

Distributed by: MWI, Boise, Idaho 83705 • www.VetOne.net

QUESTIONS? 1-800-999-0297

PRINCIPAL DISPLAY PANEL - 30 wipe canister

VETone®

VetraSeb™ CeraDerm™ CM

Wipes

Chlorhexidine Gluconate 2%, Miconazole Nitrate 2%

Antiseptic Wipes for Dogs or Cats

Net Contents: 30 Wipes